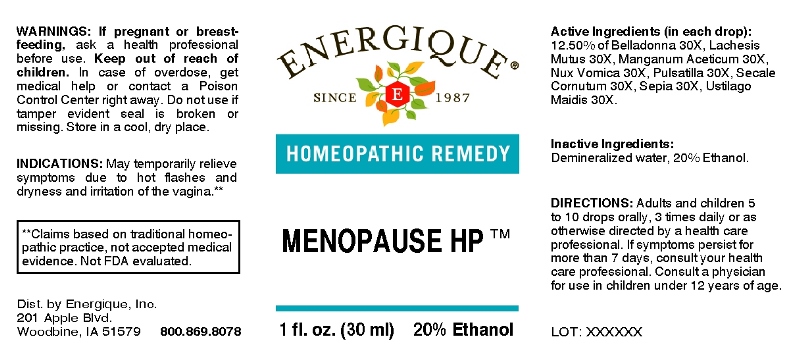 DRUG LABEL: Menopause
NDC: 44911-0248 | Form: LIQUID
Manufacturer: Energique, Inc.
Category: homeopathic | Type: HUMAN OTC DRUG LABEL
Date: 20241029

ACTIVE INGREDIENTS: ATROPA BELLADONNA 30 [hp_X]/1 mL; LACHESIS MUTA VENOM 30 [hp_X]/1 mL; MANGANESE ACETATE TETRAHYDRATE 30 [hp_X]/1 mL; STRYCHNOS NUX-VOMICA SEED 30 [hp_X]/1 mL; PULSATILLA PRATENSIS WHOLE 30 [hp_X]/1 mL; CLAVICEPS PURPUREA SCLEROTIUM 30 [hp_X]/1 mL; SEPIA OFFICINALIS JUICE 30 [hp_X]/1 mL; USTILAGO MAYDIS 30 [hp_X]/1 mL
INACTIVE INGREDIENTS: WATER; ALCOHOL

DRUG FACTS:

ACTIVE INGREDIENTS:

(in each drop): 12.50% of Belladonna 30X, Lachesis Mutus 30X, Manganum Aceticum 30X, Nux Vomica 30X, Pulsatilla (Pratensis) 30X, Secale Cornutum 30X, Sepia 30X, Ustilago Maidis 30X.

INDICATIONS:

For temporary relief of symptoms due to autonomic dysregulation, dryness and irritation of the vagina.**

**These statements are based upon traditional homeopathic practice. They have not been reviewed by the Food and Drug Administration.

WARNINGS:

If pregnant or breast-feeding, ask a health professional before use.

Keep out of reach of children. In case of overdose, get medical help or contact a Poison Control Center right away.

Do not use if tamper evident seal is broken or missing. Store in a cool, dry place.

Keep out of reach of children. In case of overdose, get medical help or contact a Poison Control Center right away.

DIRECTIONS:

Adults and children 5 to 10 drops orally, 3 times daily or as otherwise directed by a health care professional. If symptoms persist for more than 7 days, consult your health care professional. Consult a physician for use in children under 12 years of age.

INDICATIONS:

For temporary relief of symptoms due to autonomic dysregulation, dryness and irritation of the vagina.**

**These statements are based upon traditional homeopathic practice. They have not been reviewed by the Food and Drug Administration.

INACTIVE INGREDIENTS:

Demineralized water, 20% Ethanol.

QUESTIONS:

Dist. by Energique, Inc.

201 Apple Blvd

Woodbine, IA 51579 800-869-8078

PACKAGE LABEL DISPLAY:

ENERGIQUE
SINCE 1987
HOMEOPATHIC REMEDY
MENOPAUSE HP
1 fl. oz. (30 ml)